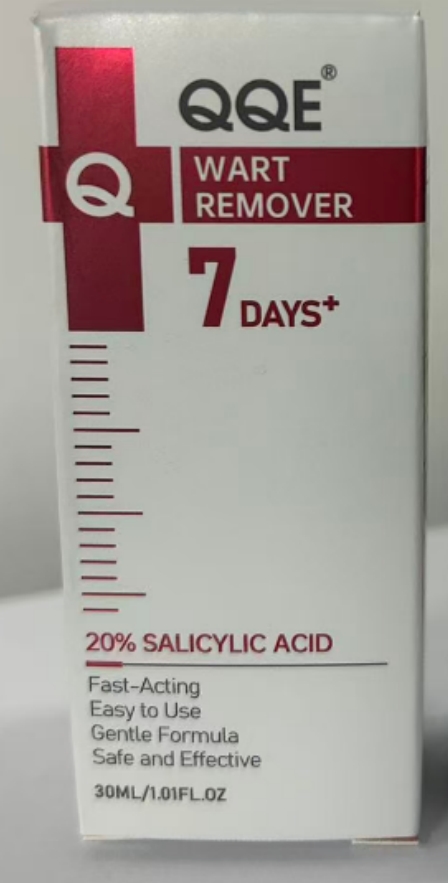 DRUG LABEL: QQE WART REMOVER
NDC: 84556-425 | Form: LIQUID
Manufacturer: Hainan Shengtaizhuo International Information Development Co., LTD
Category: otc | Type: HUMAN OTC DRUG LABEL
Date: 20251007

ACTIVE INGREDIENTS: SALICYLIC ACID 2 mg/30 mL
INACTIVE INGREDIENTS: BORNEOL; GLYCERIN; PODOFILOX; WATER; ALLANTOIN; BISABOLOL

PURPOSE

WART REMOVER

ACTIVE INGREDIENT

20% SALICYLIC ACID

INDICATIONS AND USAGE

1. Clean the affected area.
2. Dip a cotton swab in a small amount of the liquid medicine and apply it only to the surface of the wart, avoiding contact with the surrounding skin.
3. You can apply moisturizing cream around the wart.
4. Let it air dry naturally after application and avoid friction or covering with clothing.

WARNINGS

For external use only.For external use only Keep away from fire and flame

KEEP OUT OF REACH OF CHILDREN

If swallowed, get medical help or contact a Poison Control Center right away.

WHEN USING

1. Do not apply on other parts of the body, For topical use only on the scalp
2. Avoid contact with the eyes in case of accidental contact rinse eyes with large arnounts of cool tap water.

DO NOT USE

You are under 18 years old. Do not use it for infants and children. Red, inflamed, infected, itchy or painful scalp.
You are using other medications on the affected area. If you have heart disease, consult your doctor before using.

STOP USE

Chest pain, rapid heart beat, faintness, or dizziness occurs sudden, unexplained weight gain occurs,your hands or feet swell.

DOSAGE AND ADMINISTRATION

Twice each day,4 sprays (1ml)each time. 30 days supply

INACTIVE INGREDIENT

WATER, BORNEOL, GLYCERIN, PODOFILOX, POLYETHYLENE GLYCOL, BISABOLOL, ALLANTOIN.